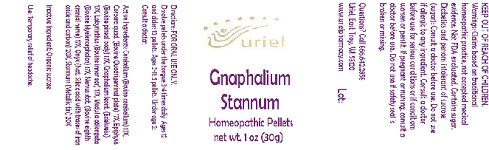 DRUG LABEL: Gnaphalium Stannum
NDC: 48951-5028 | Form: PELLET
Manufacturer: Uriel Pharmacy Inc.
Category: homeopathic | Type: HUMAN OTC DRUG LABEL
Date: 20180426

ACTIVE INGREDIENTS: BOS TAURUS CEREBELLUM 17 [hp_X]/1 1; BOS TAURUS BRAIN 17 [hp_X]/1 1; BOS TAURUS PINEAL GLAND 17 [hp_X]/1 1; PSEUDOGNAPHALIUM LUTEOALBUM LEAF 17 [hp_X]/1 1; SUS SCROFA EAR 17 [hp_X]/1 1; BOS TAURUS NERVE 17 [hp_X]/1 1; BIFENTHRIN 20 [hp_X]/1 1; TIN 20 [hp_X]/1 1
INACTIVE INGREDIENTS: SUCROSE

Gnaphalium Stannum

INDICATIONS AND USAGE

Directions: FOR ORAL USE ONLY.

DOSAGE AND ADMINISTRATION

Dissolve pellets under the tongue 3-4 times daily. Ages 12 and older: 10 pellets. Ages 2-11: 5 pellets. Under age 2: Consult a doctor.

ACTIVE INGREDIENT

Active Ingredients: Cerebellum (Bovine cerebellum) 17X, Corpora quad. (Bovine Quadrigeminal plate) 17X, Epiphysis (Bovine pineal body) 17X, Gnaphalium leont. (Edelweiss) 17X, Labyrinthus (Bovine inner ear) 17X, Medulla oblongata (Bovine Myelencephalon) 17X, Nervus stat. (Bovine eighth cranial nerve) 17X, Onyx (Nat. Silicic acid with traces of iron oxide and carbon) 20X, Stannum (Metallic tin) 20X

Inactive Ingredient: Organic sucrose

PURPOSE

Use: Temporary relief of headache.

KEEP OUT OF REACH OF CHILDREN.

WARNINGS

Warnings: Claims based on traditional homeopathic practice, not accepted medical evidence. Not FDA evaluated. Contains sugar. Diabetics and persons intolerant of sucrose (sugar): Consult a doctor before use. Do not use if allergic to any ingredient. Consult a doctor before use for serious conditions or if conditions worsen or persist. If pregnant or nursing, consult a doctor before use. Do not use if safety seal is broken or missing.

QUESTIONS

Questions? Call 866.642.2858 Uriel, East Troy, WI 53120 www.urielpharmacy.com